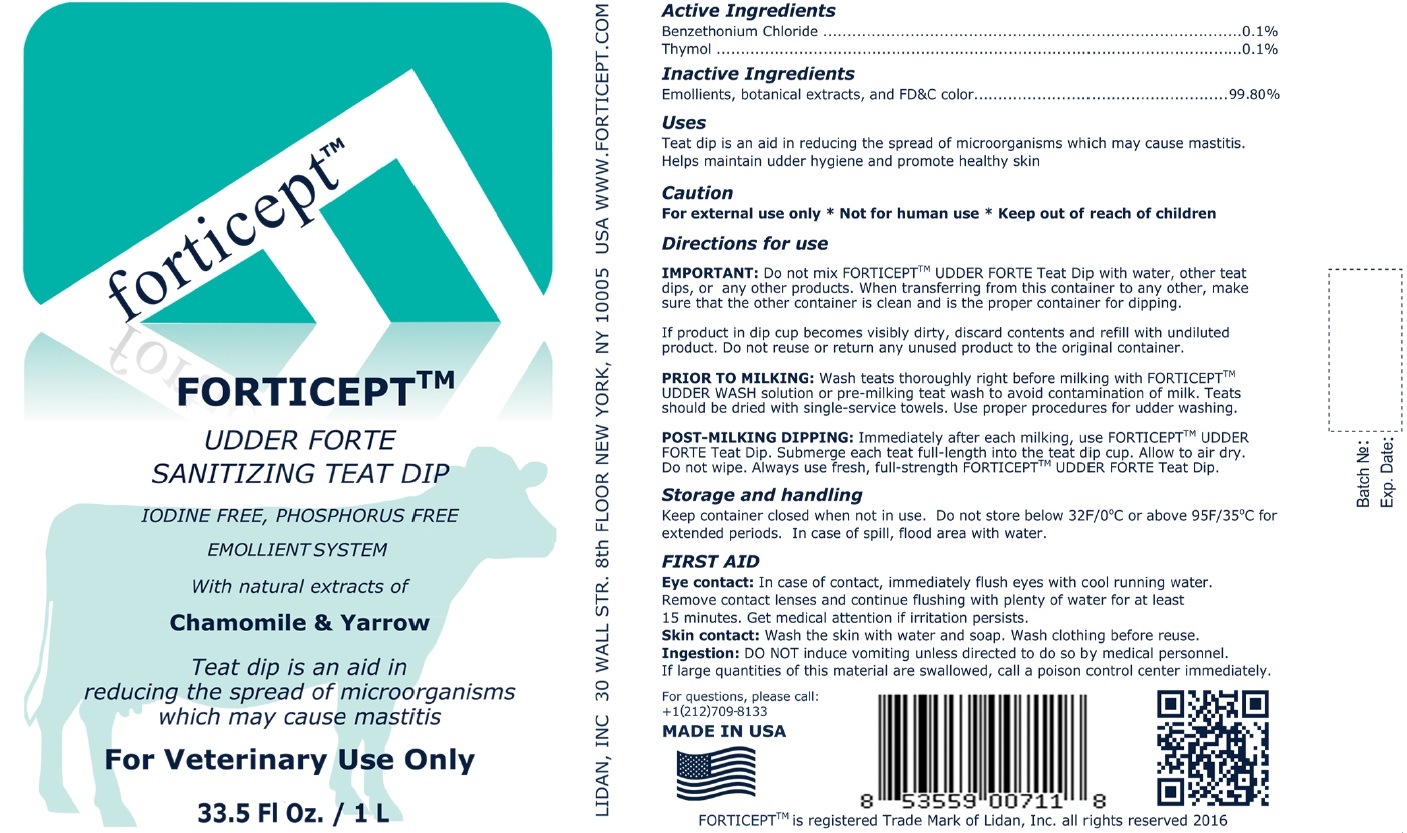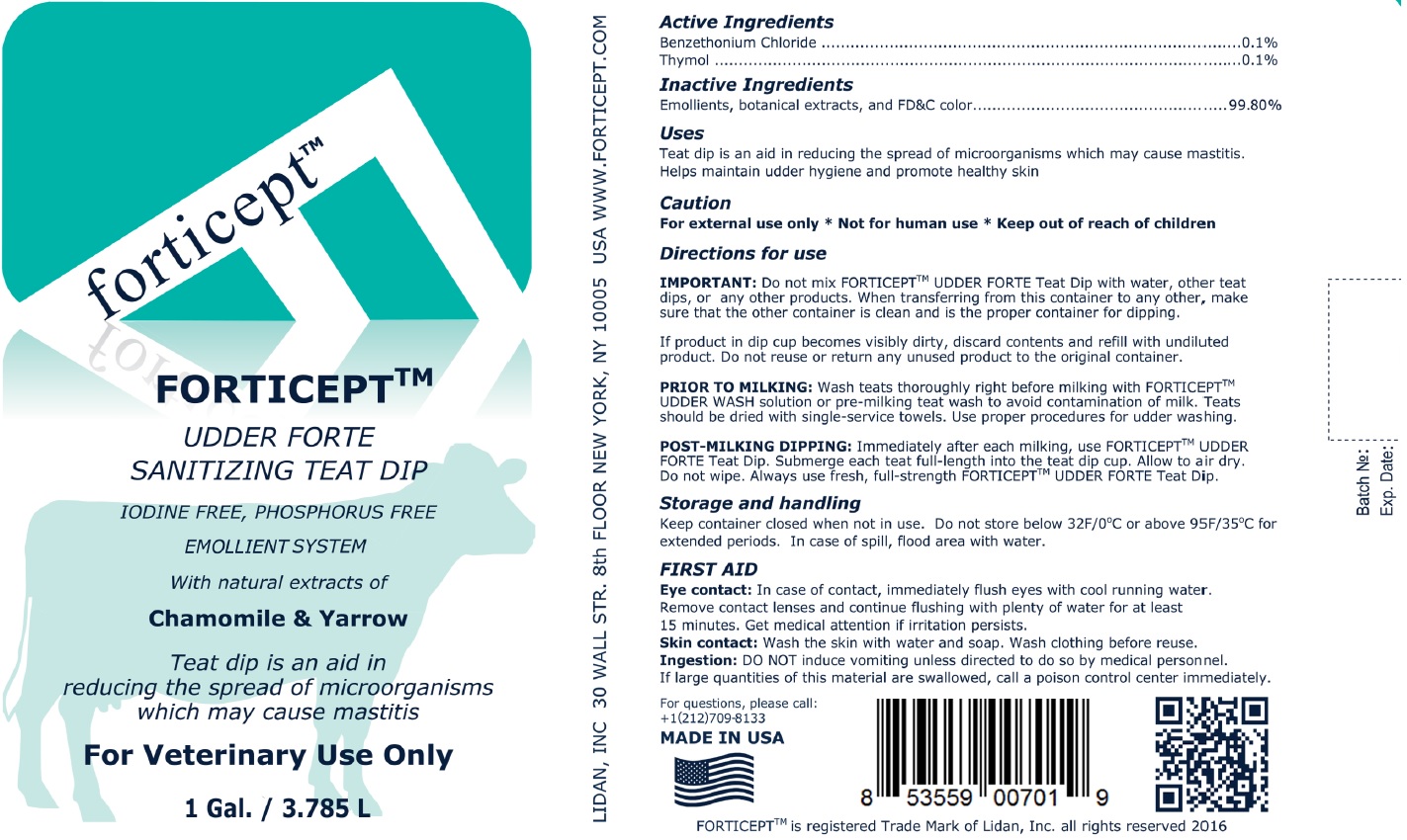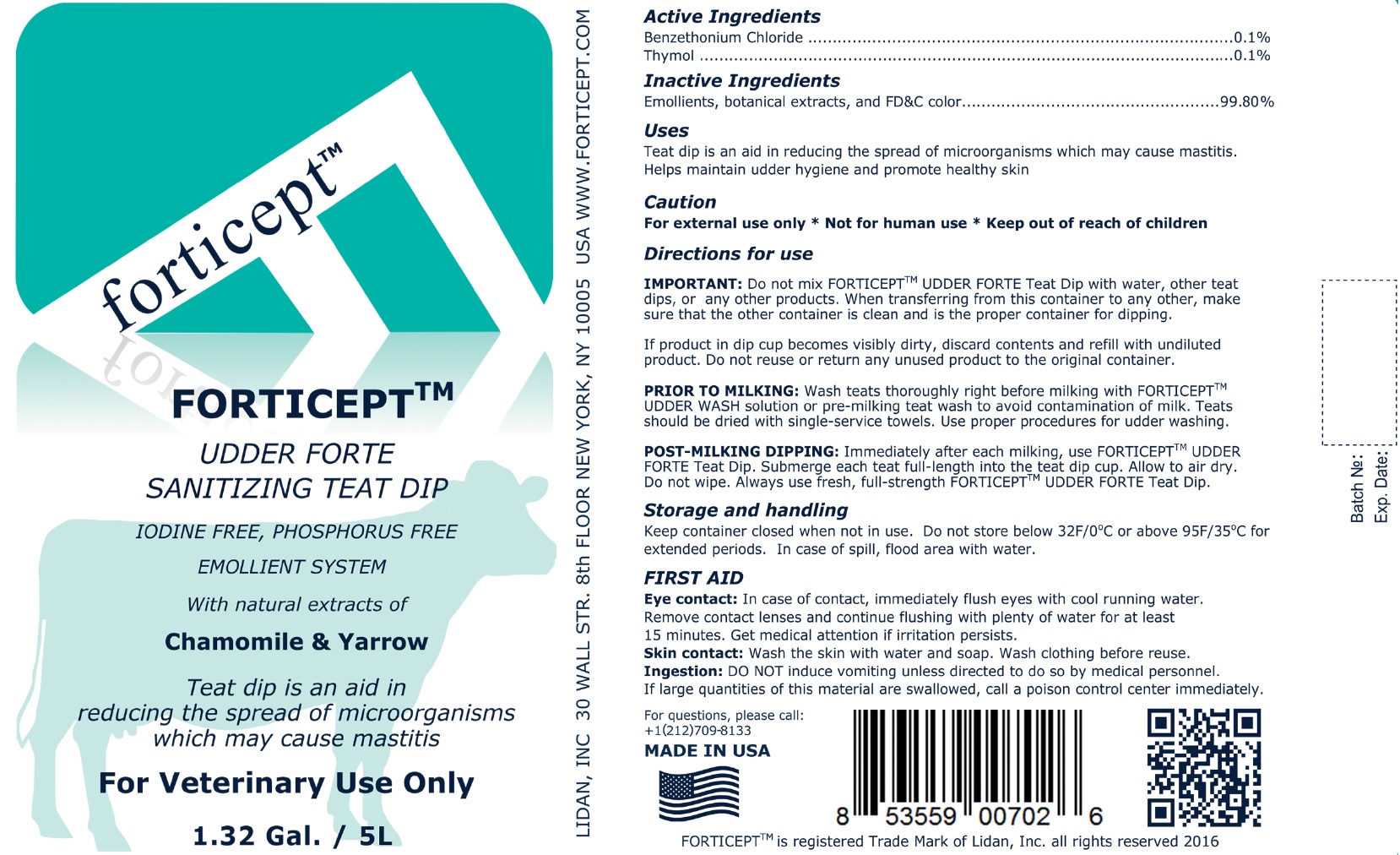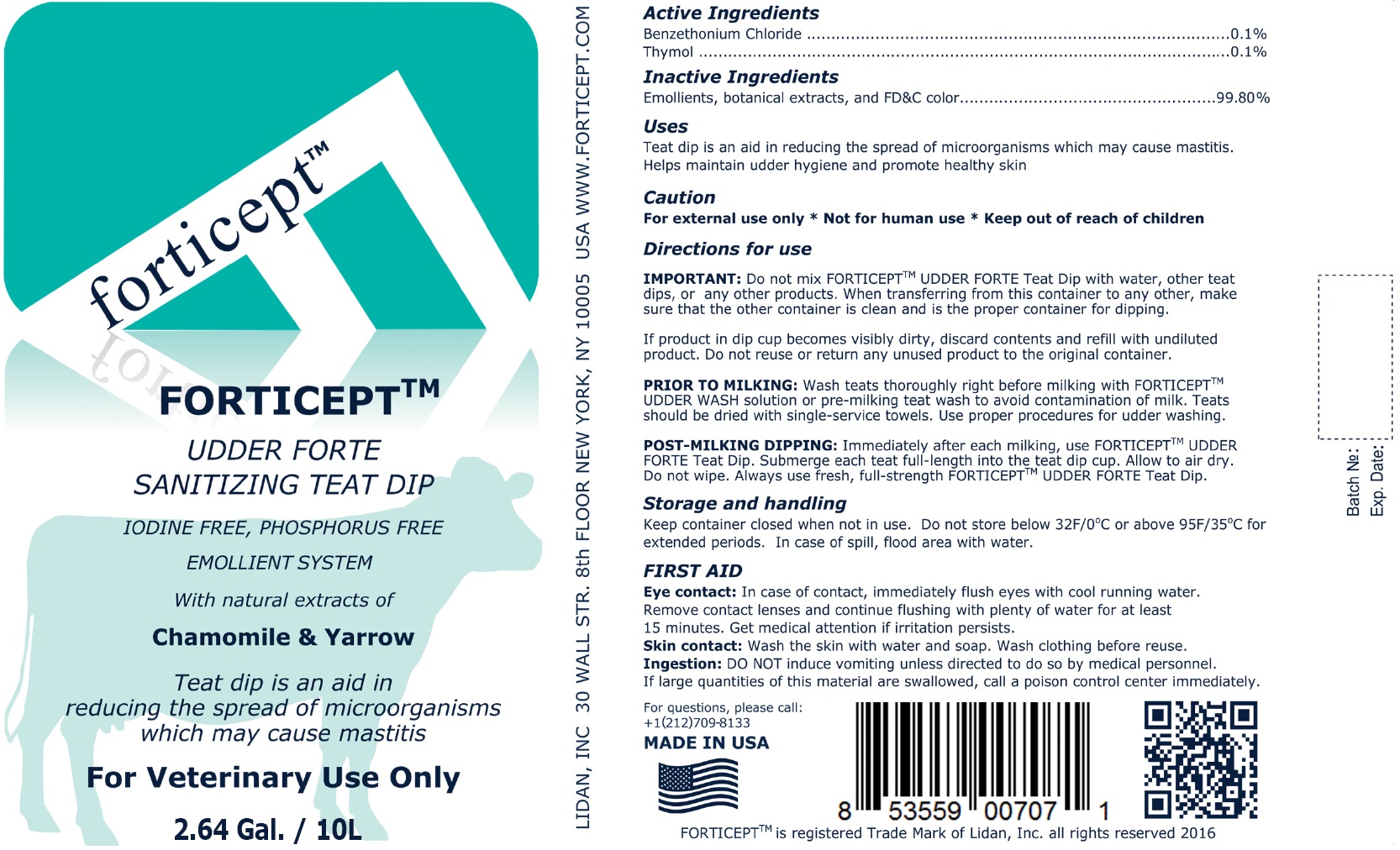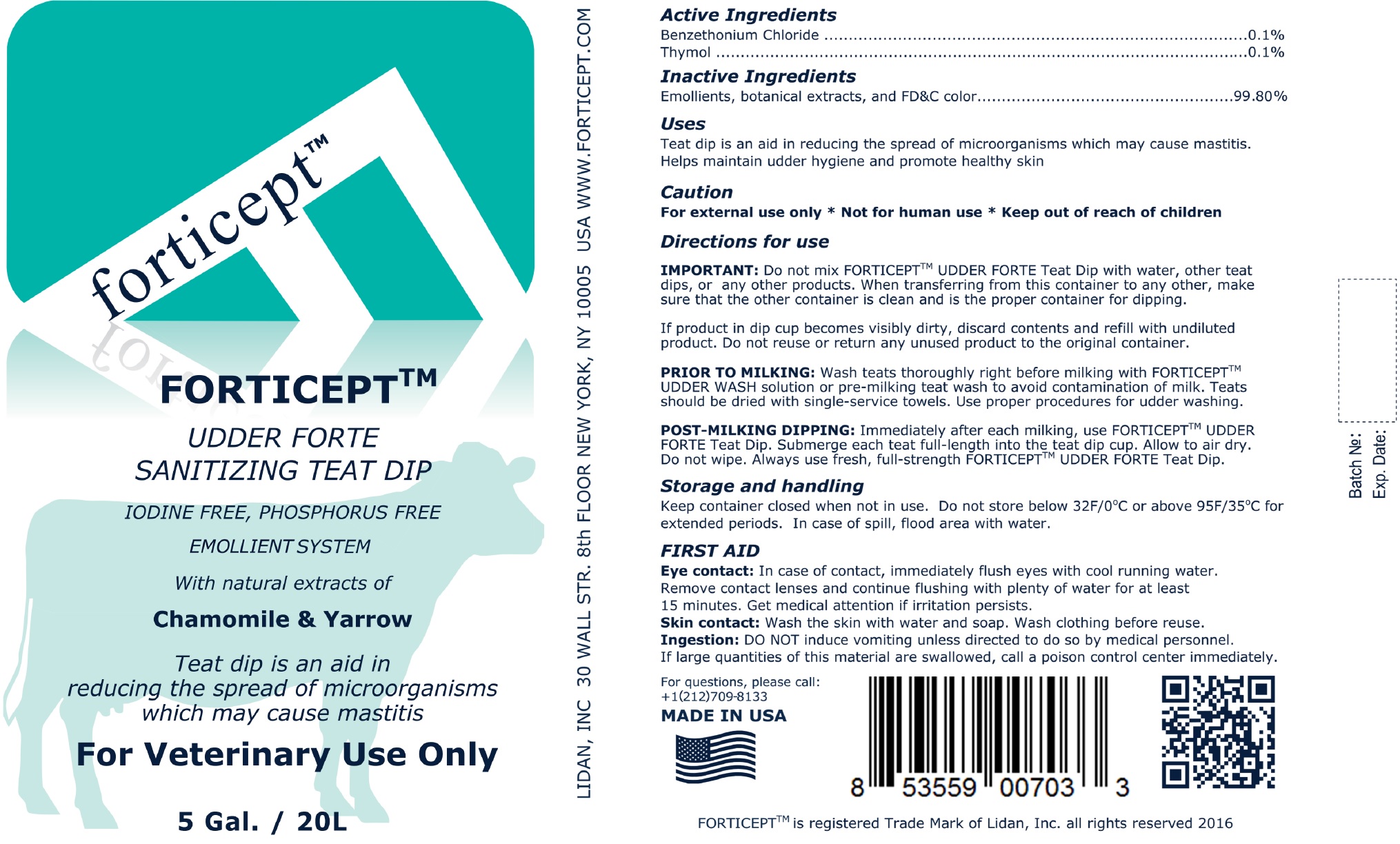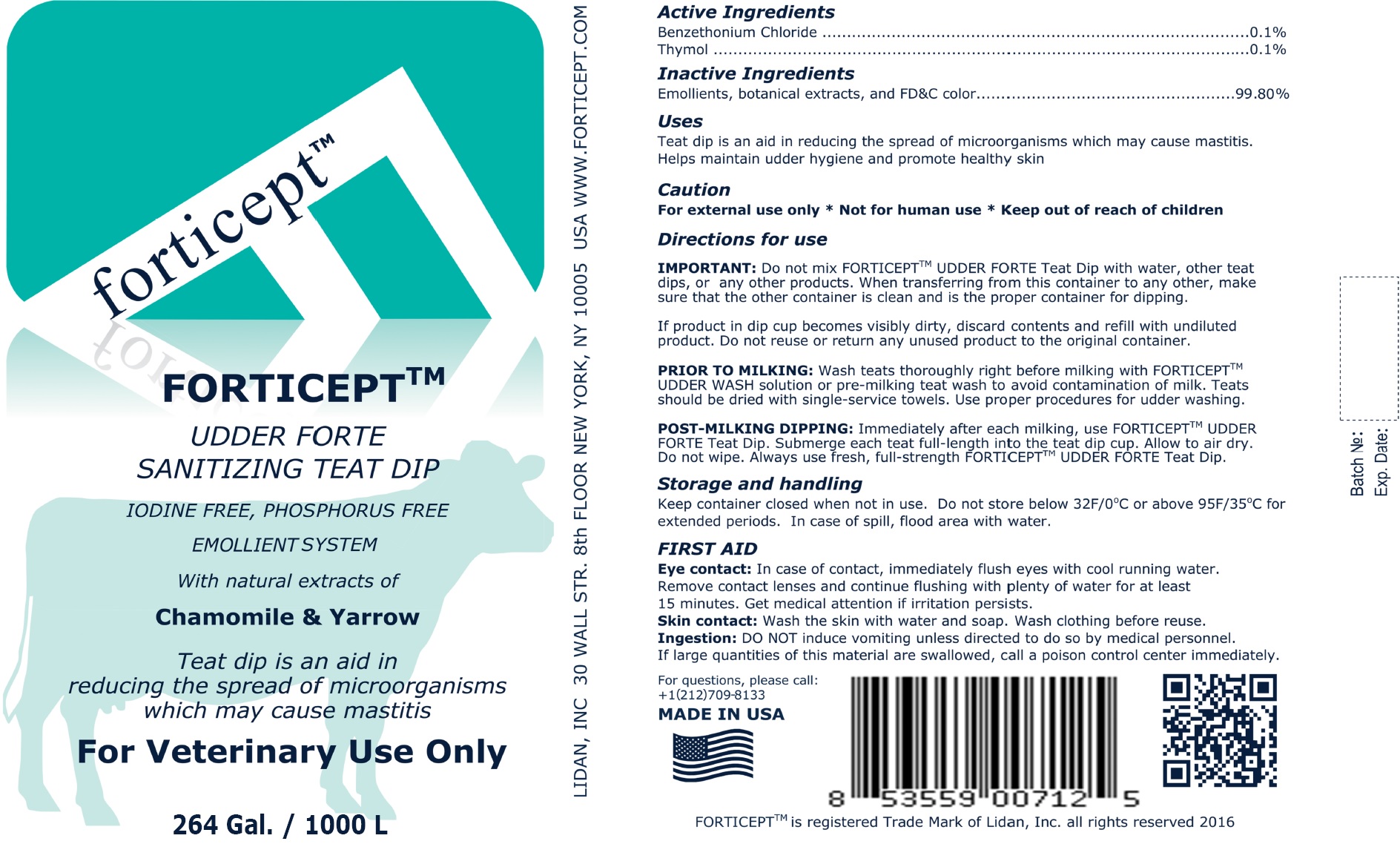 DRUG LABEL: Forticept Udder Forte Sanitizing Teat Dip
NDC: 72127-0209 | Form: EMULSION
Manufacturer: LIDAN, INC.
Category: animal | Type: OTC ANIMAL DRUG LABEL
Date: 20240927

ACTIVE INGREDIENTS: BENZETHONIUM CHLORIDE 1 g/1 L; THYMOL 1 g/1 L

Forticept Udder Forte Sanitizing Teat Dip

Active Ingredients

Benzethonium Chloride 0.1%

Thymol 0.1%

Inactive Ingredients

Emollients, botanical extracts, and FD&C color...99.80%

Uses

Teat dip is an aid in reducing the spread of microorganisms which may cause mastitis.

Helps maintain udder hygiene and promote healthy skin

Caution

For external use only * Not for human use

Directions for use

IMPORTANT: Do not mix FORTICEPTTM UDDER FORTE Teat Dip with water, other teat dips, or any other products. When transferring from this container to any other, make sure that the other container is clean and is the proper container for dipping.

If product in dip cup becomes visibly dirty, discard contents and refill with undiluted product. Do not reuse or return any unused product to the original container.

PRIOR TO MILKING: Wash teats thoroughly right before milking with FORTICEPTTM UDDER WASH solution or pre-milking teat wash to avoid contamination of milk. Teats should be dried with single-service towels. Use proper procedures for udder washing.

POST-MILKING DIPPING: Immediately after each milking, use FORTICEPTTM UDDER FORTE Teat Dip. Submerge each teat full-length into the teat dip cup. Allow to air dry. Do not wipe. Always use fresh, full-strength FORTICEPTTM UDDER FORTE Teat Dip.

Storage and handling

Keep container closed when not in use. Do not store below 32F/0°C or above 95F/35°C for extended periods. In case of spill, flood area with water.

FIRST AID

Eye contact: In case of contact, immediately flush eyes with cool running water.

Remove contact lenses and continue flushing with plenty of water for at least 15 minutes. Get medical attention if irritation persists.

Skin contact: Wash the skin with water and soap. Wash clothing before reuse.

Ingestion: DO NOT induce vomiting unless directed to do so by medical personnel.

If large quantities of this material are swallowed, call a poison control center immediately.

Questions

For questions, please call:

+1(212)709-8133